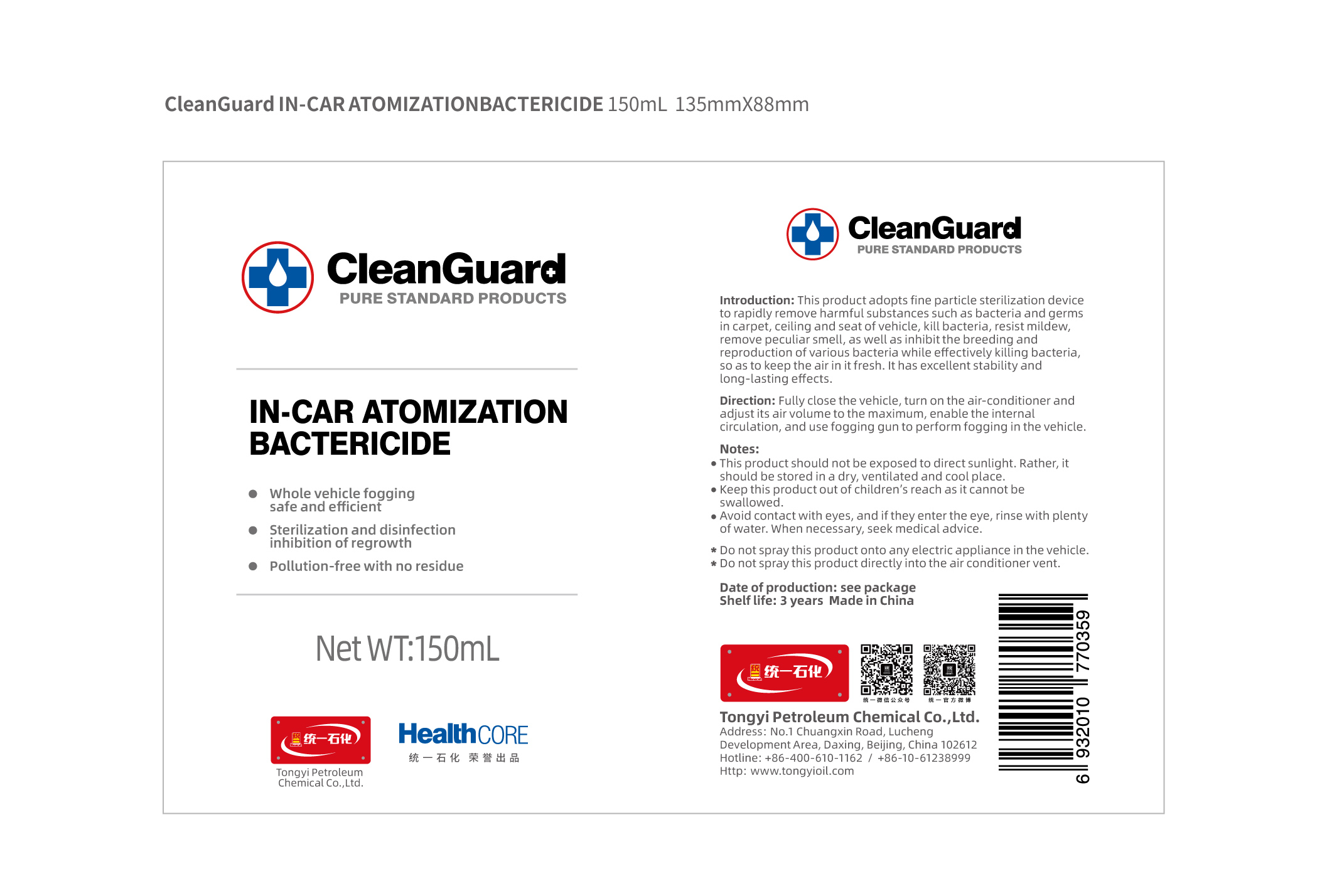 DRUG LABEL: TongYi CleanGuard In-car Atomization Bactericide
NDC: 73681-4501 | Form: SPRAY
Manufacturer: Tongyi Petroleum Chemical Co., Ltd.
Category: otc | Type: HUMAN OTC DRUG LABEL
Date: 20200401

ACTIVE INGREDIENTS: ALCOHOL 44.25 mL/150 mL
INACTIVE INGREDIENTS: BENZALKONIUM CHLORIDE 0.75 mL/150 mL; WATER 105 mL/150 mL

TongYi, In-car Atomization Bactericide, 150mL *24

Active ingredient

Ethanol

Inactive ingredient

Water

Benzalkonium chloride

Purpose

This product adopts fine particle sterilization device to rapidly remove harmful substances such as bacteria and germs in carpet, ceiling and seat of vehicle, kill bacteria, resist mildew, remove peculiar smell, as well as inhibit the breeding and reproduction of various bacteria while effectively killing bacteria, so as to keep the air in it fresh. It has excellent stability and long-lasting effects.

When using

This product adopts fine particle sterilization device to rapidly remove harmful substances such as bacteria and germs in carpet, ceiling and seat of vehicle, kill bacteria, resist mildew, remove peculiar smell, as well as inhibit the breeding and reproduction of various bacteria while effectively killing bacteria, so as to keep the air in it fresh. It has excellent stability and long-lasting effects.

Do not use

Use only as directed.
Do not use for cases not directed.

Stop use

Stop use if the product's volatile gases cause discomfort, or if you experience respiratory irritation such as cough, asthma, or difficulty breathing.

Ask doctor

If using the product causes serious discomfort, ask or see your doctor.

Ask doctor/pharmacist

If using the product causes serious discomfort, ask or see your doctor/pharmacist.

Keep out of reach of children

Questions

Please contact with us at the phone number +86-10-61238999 when you have any questions.

Pregnancy or breast feeding

Pregnant or breast feeding women shall follow doctor advice.

Indications & usage

Fully close the vehicle, turn on the air-conditioner and adjust its air volume to the maximum, enable the internal circulation, and use fogging gun to perform fogging in the vehicle.

Dosage & administration

Use it as needed, after following the usage instructions.

For external use only.

Dosage forms & strengths

This product is spray dosage form.
The active ingredient strength is 70%.

Warnings

This product should not be exposed to direct sunlight. Rather, it should be stored in a dry, ventilated and cool place.
Keep this product out of children’s reach as it cannot be swallowed.
Avoid contact with eyes, and if they enter the eye, rinse with plenty of water. When necessary, seek medical advice.

Do not spray this product onto any electric appliance in the vehicle.

Do not spray this product directly into the air conditioner vent.